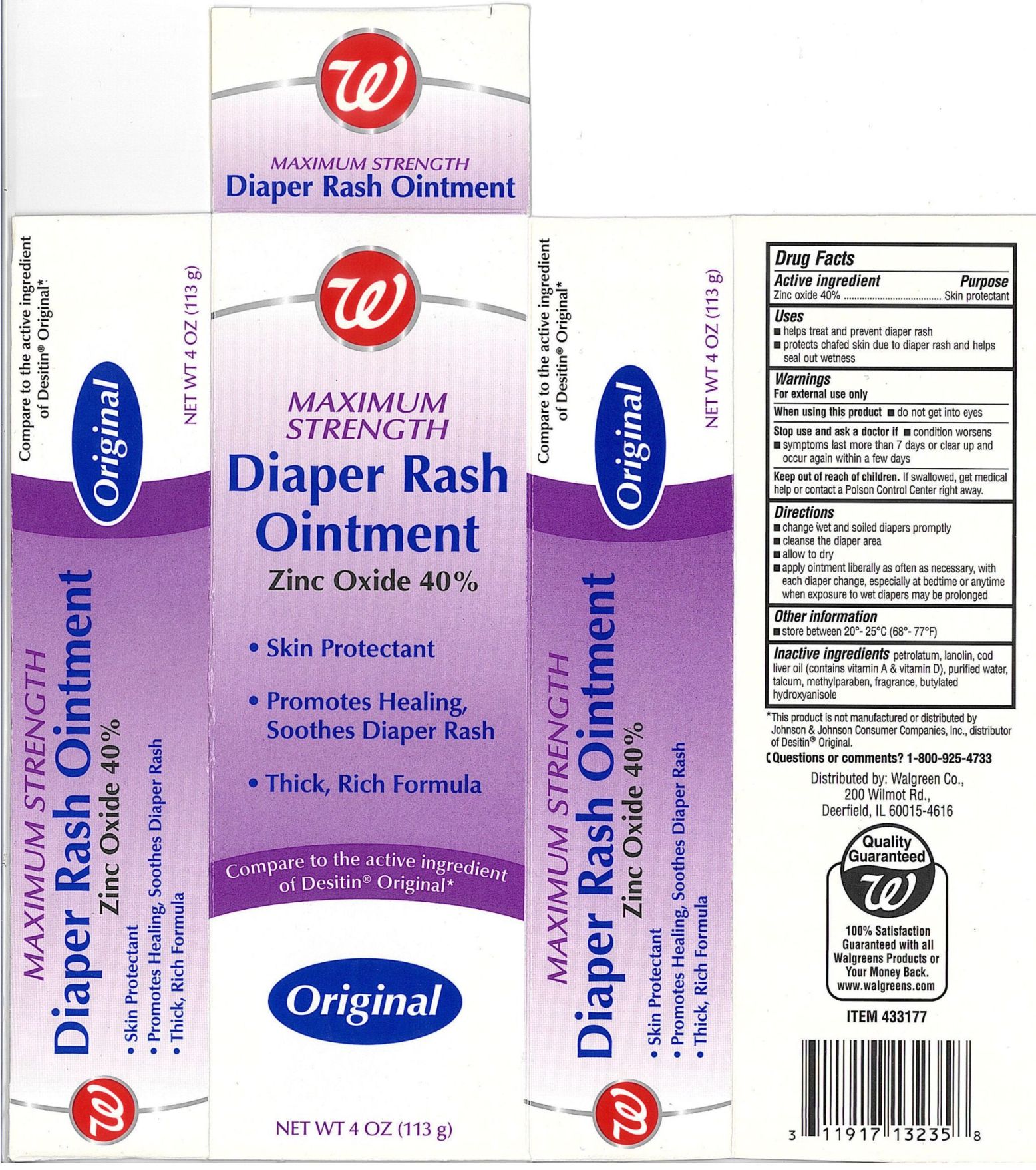 DRUG LABEL: Walgreen Maximum Strength Diaper Rash
NDC: 0363-0402 | Form: OINTMENT
Manufacturer: WALGREEN COMPANY
Category: otc | Type: HUMAN OTC DRUG LABEL
Date: 20110701

ACTIVE INGREDIENTS: ZINC OXIDE 400 mg/1 g
INACTIVE INGREDIENTS: PETROLATUM; LANOLIN; METHYLPARABEN; BUTYLATED HYDROXYANISOLE; WATER; TALC; COD LIVER OIL

drug facts

Active ingredient Purpose
Zinc Oxide. 40%.......................................Skin protectant

Uses
- helps treat and prevent diaper rash
- protects chafed skin due to diaper rash and helps seal out wetness

Keep out of the reach of children.
If swallowed, get medical help or contact
a Poison Control Center right away.

Uses
- helps treat and prevent diaper rash
- protects chafed skin due to diaper rash and helps seal out wetness

Warnings
For external use only.
When using this product - do not get into eyes
Stop use and ask a doctor if:
- condition worsens - symptoms last more than 7 days or clear
up and occur again within a few days.
Keep out of the reach of children. If swallowed get medical help or contact a Poison Control Center right away

Directions
- change wet and soiled diapers promptly
- cleanse the diaper area
- allow to dry
- apply ointment liberally as often as necessary, with each diaper change,
especially at bedtime or anytime when exposure to wet diapers may be prolonged
Other information
Store at 20 degrees to 25 degrees C (68 degrees to 77 degrees F)

Inactive Ingredients
petrolatum, lanolin, cod liver oil (contains vitamin A and vitamin D),
purified water, talcum, methylparaben, fragrance, butylated hydroxyanisole